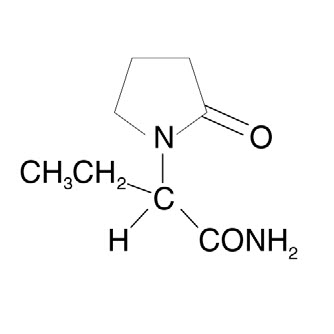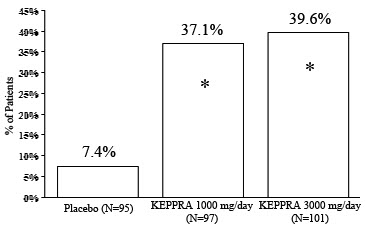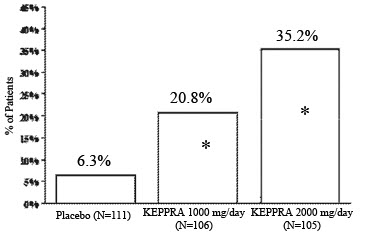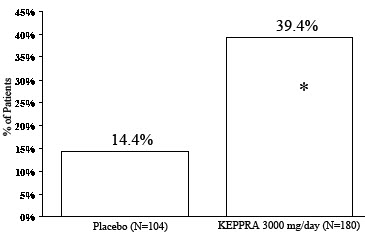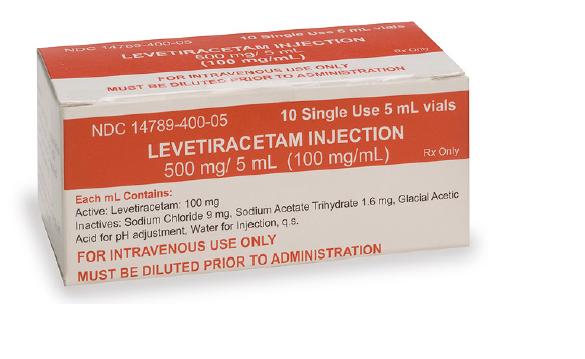 DRUG LABEL: Levetiracetam
NDC: 14789-400 | Form: INJECTION, SOLUTION
Manufacturer: Nexus Pharmaceuticals Inc
Category: prescription | Type: HUMAN PRESCRIPTION DRUG LABEL
Date: 20110809

ACTIVE INGREDIENTS: LEVETIRACETAM 100 mg/1 mL
INACTIVE INGREDIENTS: SODIUM CHLORIDE 9 mg/1 mL; SODIUM ACETATE 1.6 mg/1 mL; ACETIC ACID; WATER

HIGHLIGHTS OF PRESCRIBING INFORMATION

These highlights do not include all the information needed to use LEVETIRACETAM safely and effectively.
See full prescribing information for LEVETIRACETAM.
Levetiracetam Injection for intravenous use.
Initial U.S. Approval : 1999

RECENT MAJOR CHANGES

Indications and Usage,

- Myoclonic Seizures In Patients With Juvenile Myoclonic Epilepsy (1.2) [09/2007]
- Dosage and Administration, (2.2) [05/2008]
- Warnings and Precautions, (5.1, 5.3) [05/2008]

1 INDICATIONS AND USAGE

LEVETIRACETAM injection is an antiepileptic drug indicated for adjunct therapy in adults (≥16 years of age) with the following seizure types when oral administration of LEVETIRACETAM is temporarily not feasible:

- Partial Onset Seizures (1.1)
- Myoclonic Seizures in Patients with Juvenile Myoclonic Epilepsy (1.2)

2 DOSAGE AND ADMINISTRATION

LEVETIRACETAM injection should be diluted in 100 mL of a compatible diluent and administered intravenously as a 15-minute infusion (2.1).

Initial Exposure To LEVETIRACETAM (2.2):

- Partial Onset Seizures: 1000 mg/day, given as twice-daily dosing (500 mg twice daily), increased as needed and as tolerated in increments of 1000 mg/day additional every 2 weeks to a maximum recommended daily dose of 3000 mg.
- Myoclonic Seizures in Patients with Juvenile Myoclonic Epilepsy: 1000 mg/day, given as twice-daily dosing (500 mg twice daily), increased by 1000 mg/day every 2 weeks to the recommended daily dose of 3000 mg. The effectiveness of doses lower than 3000 mg/day has not been adequately studied.
- Replacement Therapy (2.3): When switching from oral LEVETIRACETAM, the initial total daily intravenous dosage of LEVETIRACETAM should be equivalent to the total daily dosage and frequency of oral LEVETIRACETAM. At the end of the intravenous treatment period, the patient may be switched to equivalent daily dosage and frequency of the intravenous administration.

See full prescribing information for dosing instructions (2.5), adult patients with impaired renal function (2.6), and compatibility and stability (2.7).

3 DOSAGE FORMS AND STRENGTHS

- 500 mg/5 ml single-use vial (3)

4 CONTRAINDICATIONS

None (4)

5 WARNINGS AND PRECAUTIONS

- Neuropsychiatric Adverse Reactions: Including: 1) Somnolence and fatigue, 2) Coordination difficulties and 3) Behavioral Abnormalities (e.g., psychotic symptoms, suicide ideation, and other abnormalities). (5.1)
- Withdrawal Seizures: LEVETIRACETAM must be gradually withdrawn. (5.2)

6 ADVERSE REACTIONS

- Most common adverse reactions (difference in incidence rate is ≥5% between LEVETIRACETAM-treated patients and placebo-treated patients and occurred more frequently in LEVETIRACETAM-treated patients) include: somnolence, asthenia, infection, and dizziness (6.1) .
- Important behavioral adverse reactions (incidence of • LEVETIRACETAM-treated patients > placebo-treated patients, but <5%) include depression, nervousness, anxiety, and emotional lability (6.1) .

To Report SUSPECTED ADVERSE REACTIONS, contact Nexus Pharma at 877-913-2720 or FDA at 1-800-FDA-1088 or www.fda.gov/medwatch

8 USE IN SPECIFIC POPULATIONS

- To ensure broad program access and reach, either a healthcare provider or the patient can initiate enrollment in the North American Antieplileptic Drug Pregnancy Registry by calling (888) 233-2334 (toll free). (8.1).
- A dose adjustment is recommended for patient’s estimated creatinine clearance (8.6).

FULL PRESCRIBING INFORMATION

1 INDICATIONS AND USAGE

LEVETIRACETAM injection is an alternative for adult patients (16 years and older) when oral administration is temporarily not feasible.

1.1 Partial Onset Seizures

LEVETIRACETAM is indicated as adjunctive therapy in the treatment of partial onset seizures in adults with epilepsy.

1.2 Myoclonic Seizures in Patients with Juvenile Myoclonic Epilepsy

LEVETIRACETAM is indicated as adjunctive therapy in the treatment of myoclonic seizures in adults with juvenile myoclonic epilepsy.

2 DOSAGE AND ADMINISTRATION

2.1 General Information

LEVETIRACETAM injection is for intravenous use only and must be diluted prior to administration. LEVETIRACETAM injection (500 mg/5 mL) should be diluted in 100 mL of a compatible diluent [see Dosage and Administration (2.7)] and administered intravenously as a 15-minute IV infusion.

Product with particulate matter or discoloration should not be used.

Any unused portion of the LEVETIRACETAM injection vial contents should be discarded.

2.2 Initial Exposure to LEVETIRACETAM

LEVETIRACETAM can be initiated with either intravenous or oral administration.

Partial Onset Seizures - In clinical trials of oral LEVETIRACETAM, daily doses of 1000 mg, 2000 mg, and 3000 mg, given as twice-daily dosing, were shown to be effective. Although in some studies there was a tendency toward greater response with higher dose [see Clinical Studies (14.1)], a consistent increase in response with increased dose has not been shown. Treatment should be initiated with a daily dose of 1000 mg/day, given as twice-daily dosing (500 mg twice daily). Additional dosing increments may be given (1000 mg/day additional every 2 weeks) to a maximum recommended daily dose of 3000 mg. Doses greater than 3000 mg/day have been used in open-label studies with LEVETIRACETAM tablets for periods of 6 months and longer. There is no evidence that doses greater than 3000 mg/day confer additional benefit.

Myoclonic Seizures in Patients with Juvenile Myoclonic Epilepsy - Treatment should be initiated with a dose of 1000 mg/day, given as twice-daily dosing (500 mg twice daily). Dosage should be increased by 1000 mg/day every 2 weeks to the recommended daily dose of 3000 mg. The effectiveness of doses lower than 3000 mg/day has not been studied.

2.3 Replacement Therapy

When switching from oral LEVETIRACETAM, the initial total daily intravenous dosage of LEVETIRACETAM should be equivalent to the total daily dosage and frequency of oral LEVETIRACETAM and should be administered as a 15-minute intravenous infusion following dilution in 100 mL of a compatible diluent.

2.4 Switching to Oral Dosing

At the end of the intravenous treatment period, the patient may be switched to LEVETIRACETAM oral administration at the equivalent daily dosage and frequency of the intravenous administration.

2.5 Dosing Instructions

LEVETIRACETAM injection is for intravenous use only and must be diluted prior to administration. One vial of LEVETIRACETAM injection contains 500 mg levetiracetam (500 mg/5mL). See Table 1 for the recommended preparation and administration of LEVETIRACETAM injection to achieve a dose of 500 mg, 1000 mg, or 1500 mg.

Table 1 : Preparation and Administration of LEVETIRACETAM Injection
Dose | Withdraw Volume | Volume of Diluent | Infusion Time
500 mg | 5 mL (5 mL vial) | 100 mL | 15 minutes
1000 mg | 10 mL (two 5 mL vials) | 100 mL | 15 minutes
1500 mg | 15 mL (three 5 mL vials) | 100 mL | 15 minutes

For example, to prepare a 1000 mg dose, dilute 10 mL of LEVETIRACETAM injection in 100 mL of a compatible diluent [ see Dosage and Administration (2.7)] and administer intravenously as a 15-minute infusion.

2.6 Adult Patients with Impaired Renal Function

LEVETIRACETAM dosing must be individualized according to the patient's renal function status. Recommended doses and adjustment for dose for adults are shown in Table 2. To use this dosing table, an estimate of the patient's creatinine clearance (CLcr) in mL/min is needed. CLcr in mL/min may be estimated from serum creatinine (mg/dL) determination using the following formula:

1. For female patients

[140-age (years)] x weight (kg)

CLcr= - - - - - - - - - - - - - - - - - - - - - - x ^10.85
72 x serum creatinine (mg/dL)

^1For female patients

Table 2 : Dosing Adjustment Regimen for Adult Patients with Impaired Renal Function
Group | Creatinine Clearance; (mL/min) | Dosage; (mg) | Frequency
Normal | > 80 | 500 to 1,500 | Every 12 h
Mild | 50 to 80 | 500 to 1,000 | Every 12 h
Moderate | 30 to 50 | 250 to 750 | Every 12 h
Severe | < 30 | 250 to 500 | Every 12 h
ESRD patients using dialysis | --- | 500 to 1,000 | ^1Every 24 h
^1Following dialysis, a 250 to 500 mg supplemental dose is recommended.

2.7 Compatibility and Stability

LEVETIRACETAM injection was found to be physically compatible and chemically stable when mixed with the following diluents and antiepileptic drugs for at least 24 hours and stored in polyvinyl chloride (PVC) bags at controlled room temperature 15 to 30°C (59 to 86°F).

Diluents

Sodium chloride (0.9%) injection, USP
Lactated Ringer’s injection
Dextrose 5% injection, USP

Other Antiepileptic Drugs

Lorazepam
Diazepam

Valproate sodium

There is no data to support the physical compatibility of LEVETIRACETAM injection with antiepileptic drugs that are not listed above.

Parenteral drug products should be inspected visually for particulate matter and discoloration prior to administration whenever solution and container permit.

3 DOSAGE FORMS AND STRENGTHS

One vial of LEVETIRACETAM injection contains 500 mg levetiracetam (500 mg/5 mL).

4 CONTRAINDICATIONS

None

5 WARNINGS AND PRECAUTIONS

5.1 Neuropsychiatric Adverse Reactions

Partial Onset Seizures - In some adults experiencing partial onset seizures, LEVETIRACETAM causes the occurrence of central nervous system adverse reactions that can be classified into the following categories: 1) somnolence and fatigue, 2) coordination difficulties, and 3) behavioral abnormalities.

In controlled trials of adult patients with epilepsy experiencing partial onset seizures, 14.8% of LEVETIRACETAM-treated patients reported somnolence, compared to 8.4% of placebo patients. There was no clear dose response up to 3000 mg/day. In a study where there was no titration, about 45% of patients receiving 4000 mg/day reported somnolence. The somnolence was considered serious in 0.3% of the treated patients, compared to 0% in the placebo group. About 3% of LEVETIRACETAM-treated patients discontinued treatment due to somnolence,compared to 0.7% of placebo patients. In 1.4% of treated patients and in 0.9% of placebo patients the dose was reduced, while 0.3% of the treated patients were hospitalized due to somnolence.

In controlled trials of adult patients with epilepsy experiencing partial onset seizures, 14.7% of treated patients reported asthenia, compared to 9.1% of placebo patients. Treatment was discontinued in 0.8% of treated patients as compared to 0.5% of placebo patients. In 0.5% of treated patients and in 0.2% of placebo patients the dose was reduced.

A total of 3.4% of LEVETIRACETAM-treated patients experienced coordination difficulties, (reported as either ataxia, abnormal gait, or incoordination) compared to 1.6% of placebo patients. A total of 0.4% of patients in controlled trials discontinued LEVETIRACETAM treatment due to ataxia, compared to 0% of placebo patients. In 0.7% of treated patients and in 0.2% of placebo patients the dose was reduced due to coordination difficulties, while one of the treated patients was hospitalized due to worsening of pre-existing ataxia.

Somnolence, asthenia and coordination difficulties occurred most frequently within the first 4 weeks of treatment.

In controlled trials of patients with epilepsy experiencing partial onset seizures, 5 (0.7%) of LEVETIRACETAM-treated patients experienced psychotic symptoms compared to 1 (0.2%) placebo patient. Two (0.3%) LEVETIRACETAM-treated patients were hospitalized and their treatment was discontinued. Both events, reported as psychosis, developed within the first week of treatment and resolved within 1 to 2 weeks following treatment discontinuation. Two other events, reported as hallucinations , occurred after 1-5 months and resolved within 2-7 days while the patients remained on treatment. In one patient experiencing psychotic depression occurring within a month, symptoms resolved within 45 days while the patient continued treatment. A total of 13.3% of LEVETIRACETAM patients experienced other behavioral symptoms (reported as aggression, agitation, anger, anxiety, apathy, depersonalization, depression, emotional lability, hostility, irritability, etc.) compared to 6.2% of placebo patients. Approximately half of these patients reported these events within the first 4 weeks. A total of 1.7% of treated patients discontinued treatment due to these events, compared to 0.2% of placebo patients. The treatment dose was reduced in 0.8% of treated patients and in 0.5% of placebo patients. A total of 0.8% of treated patients had a serious behavioral event (compared to 0.2% of placebo patients) and were hospitalized.

In addition, 4 (0.5%) of treated patients attempted suicide compared to 0% of placebo patients. One of these patients completed suicide. In the other 3 patients, the events did not lead to discontinuation or dose reduction. The events occurred after patients had been treated for between 4 weeks and 6 months [see Patient Counseling Information (17)].

Myoclonic Seizures - During clinical development, the number of patients with myoclonic seizures exposed to LEVETIRACETAM was considerably smaller than the number with partial seizures. Therefore, under-reporting of certain adverse reactions was more likely to occur in the myoclonic seizure population. In some patients experiencing myoclonic seizures, LEVETIRACETAM causes somnolence and behavioral abnormalities. It is expected that the events seen in partial seizure patients would occur in patients with JME.

In the double-blind, controlled trial in patients with juvenile myoclonic epilepsy experiencing myoclonic seizures, 11.7% of LEVETIRACETAM-treated patients experienced somnolence compared to 1.7% of placebo patients. No patient discontinued treatment as a result of somnolence. In 1.7% of LEVETIRACETAM-treated patients and in 0% of placebo patients the dose was reduced as a result of somnolence.

Non-psychotic behavioral disorders (reported as aggression and irritability) occurred in 5% of the LEVETIRACETAM-treated patients compared to 0% of placebo patients. Non-psychotic mood disorders (reported as depressed mood, depression, and mood swings) occurred in 6.7% of LEVETIRACETAM-treated patients compared to 3.3% of placebo patients. A total of 5.0% of LEVETIRACETAM-treated patients had a reduction in dose or discontinued treatment due to behavioral or psychiatric events (reported as anxiety, depressed mood, depression, irritability, and nervousness), compared to 1.7% of placebo patients.

5.2 Withdrawal Seizures

Antiepileptic drugs, including LEVETIRACETAM, should be withdrawn gradually to minimize the potential of increased seizure frequency.

5.3 Hematologic Abnormalities

Partial Onset Seizures - Minor, but statistically significant, decreases compared to placebo in total mean RBC count (0.03 x 106/mm^3), mean hemoglobin (0.09 g/dL), and mean hematocrit (0.38%), were seen in LEVETIRACETAM-treated patients in controlled trials.

A total of 3.2% of treated and 1.8% of placebo patients had at least one possibly significant (≤2.8 x 109/L) decreased WBC, and 2.4% of treated and 1.4% of placebo patients had at least one possibly significant (≤1.0 x 109/L) decreased neutrophil count. Of the treated patients with a low neutrophil count, all but one rose towards or to baseline with continued treatment. No patient was discontinued secondary to low neutrophil counts.

Juvenile Myoclonic Epilepsy - Although there were no obvious hematologic abnormalities observed in patients with JME, the limited number of patients makes any conclusion tentative. The data from the partial seizure patients should be considered to be relevant for JME patients.

5.4 Hepatic Abnormalities

There were no meaningful changes in mean liver function tests (LFT) in controlled trials in adult patients; lesser LFT abnormalities were similar in drug and placebo treated patients in controlled trials (1.4%). No patients were discontinued from controlled trials for LFT abnormalities except for 1 (0.07%) adult epilepsy patient receiving open treatment.

5.5 Laboratory Tests

Although most laboratory tests are not systematically altered with LEVETIRACETAM treatment, there have been relatively infrequent abnormalities seen in hematologic parameters and liver function tests.

6 ADVERSE REACTIONS

6.1 Clinical Studies Experience

Because clinical trials are conducted under widely varying conditions, adverse reaction rates observed in the clinical trials of a drug cannot be directly compared to rates in the clinical trials of another drug and may not reflect the rates observed in practice.

The adverse reactions that result from LEVETIRACETAM injection use include all of those reported for LEVETIRACETAM tablets and oral solution. Equivalent doses of intravenous (IV) levetiracetam and oral levetiracetam result in equivalent Cmax, Cmin, and total systemic exposure to levetiracetam when the IV levetiracetam is administered as a 15 minute infusion. The prescriber should be aware that the adverse reaction incidence figures in the following tables, obtained when LEVETIRACETAM was added to concurrent AED therapy, cannot be used to predict the frequency of adverse experiences in the course of usual medical practice where patient characteristics and other factors may differ from those prevailing during clinical studies.Similarly, the cited frequencies cannot be directly compared with figures obtained from other clinical investigations involving different treatments, uses, or investigators. An inspection of these frequencies, however, does provide the prescriber with one basis to estimate the relative contribution of drug and non-drug factors to the adverse reaction incidences in the population studied.

Partial Onset Seizures - In well-controlled clinical studies using LEVETIRACETAM tablets in adults with partial onset seizures, the most frequently reported adverse reactions in patients receiving LEVETIRACETAM in combination with other AEDs, not seen at an equivalent frequency among placebo-treated patients, were somnolence, asthenia, infection and dizziness. Of the most frequently reported adverse reactions in placebo-controlled studies using LEVETIRACETAM tablets in adults experienc ing partial onset seizures, asthenia, somnolence and dizziness appeared to occur predominantly during the first 4 weeks of treatment with LEVETIRACETAM.

Table 3 lists treatment-emergent adverse reactions that occurred in at least 1% of adult epilepsy patients treated with LEVETIRACETAM tablets participating in placebo-controlled studies and were numerically more common than in patients treated with placebo. In these studies, either LEVETIRACETAM or placebo was added to concurrent AED therapy. Adverse reactions were usually mild to moderate in intensity.

Table 3: Incidence (%) of Treatment-Emergent Adverse Reactions in Placebo-Controlled, Add-On Studies in Adults Experiencing Partial Onset Seizures by Body System (Adverse Reactions Occurred in at Least 1% of LEVETIRACETAM-Treated Patients and Occurred More Frequently than Placebo-Treated Patients)
Body System/; Adverse Reaction | LEVETIRACETAM; (N=769); % | Placebo; (N=439); %
Body as a Whole
Asthenia | 15 | 9
Headache | 14 | 13
Infection | 13 | 8
Pain | 7 | 6
Digestive System
Anorexia | 3 | 2
Nervous System
Somnolence | 15 | 8
Dizziness | 9 | 4
Depression | 4 | 2
Nervousness | 4 | 2
Ataxia | 3 | 1
Vertigo | 3 | 1
Amnesia | 2 | 1
Anxiety | 2 | 1
Hostility | 2 | 1
Paresthesia | 2 | 1
Emotional Lability | 2 | 0
Respiratory System
Pharyngitis | 6 | 4
Rhinitis | 4 | 3
Cough Increased | 2 | 1
Sinusitis | 2 | 1
Special Senses
Diplopia | 2 | 1

Myoclonic Seizures - Although the pattern of adverse reactions in this study seems somewhat different from that seen in patients with partial seizures, this is likely due to the much smaller number of patients in this study compared to partial seizure studies. The adverse reaction pattern for patients with JME is expected to be essentially the same as for patients with partial seizures.

In the well-controlled clinical study using LEVETIRACETAM tablets in patients with myoclonic seizures, the most frequently reported adverse reactions in patients using LEVETIRACETAM in combination with other AEDs, not seen at an equivalent frequency among placebo-treated patients, were somnolence, neck pain, and pharyngitis.

Table 4 lists treatment-emergent adverse reactions that occurred in at least 5% of juvenile myoclonic epilepsy patients experiencing myoclonic seizures treated with LEVETIRACETAM tablets and were numerically more common than in patients treated with placebo. In this study, either LEVETIRACETAM or placebo was added to concurrent AED therapy. Adverse reactions were usually mild to moderate in intensity.

Table 4: Incidence (%) of Treatment-Emergent Adverse Reactions in a Placebo-Controlled, Add-On Study in Patients with Myoclonic Seizures by Body System (Adverse Reactions Occurred in at Least 5% of LEVETIRACETAM-Treated Patients and Occurred More Frequently than Placebo-Treated Patients)
Body System/; Adverse Reaction | LEVETIRACETAM; (N=60); % | Placebo; (N=60); %
Ear and labyrinth disorders
Vertigo | 5 | 3
Infections and infestations
Pharyngitis | 7 | 0
Influenza | 5 | 2
Musculoskeletal and connective tissue disorders
Neck pain | 8 | 2
Nervous System disorders
Somnolence | 12 | 2
Psychiatric disorders
Depression | 5 | 2

Discontinuation or Dose Reduction in Well-Controlled Clinical Studies

Partial Onset Seizures - In well-controlled adult clinical studies using LEVETIRACETAM tablets, 15.0% of patients receiving LEVETIRACETAM and 11.6% receiving placebo either discontinued or had a dose reduction as a result of an adverse event. Table 5 lists the most common (>1%) adverse reactions that resulted in discontinuation or dose reduction and that occurred more frequently in LEVETIRACETAM-treated patients than in placebo-treated patients.

Table 5: Adverse Reactions that Most Commonly Resulted in Discontinuation or Dose Reduction that Occurred More Frequently in LEVETIRACETAM-Treated Patients in Placebo-Controlled Studies in Adult Patients Experiencing Partial Onset Seizures
Adverse Reaction | LEVETIRACETAM; (N=769); n (%) | Placebo; (N=439); n (%)
Asthenia | 10 (1.3%) | 3 (0.7%)
Dizziness | 11 (1.4%) | 0
Somnolence | 34 (4.4%) | 7 (1.6%)

Myoclonic Seizures - In the placebo-controlled study using LEVETIRACETAM tablets, 8.3% of patients receiving LEVETIRACETAM and 1.7% receiving placebo either discontinued or had a dose reduction as a result of an adverse event. The adverse reactions that led to discontinuation or dose reduction in the well-controlled study and that occurred more frequently in LEVETIRACETAM-treated patients than in placebo-treated patients are presented in Table 6.

Table 6: Adverse Reactions that Resulted in Discontinuation or Dose Reduction that Occurred More Frequently in LEVETIRACETAM-Treated Patients in the Placebo-Controlled Study in Patients with Juvenile Myoclonic Epilepsy
Adverse Reaction | LEVETIRACETAM; (N=60); n (%) | Placebo; (N=60); n (%)
Anxiety | 2 (3.3%) | 1 (1.7%)
Depressed mood | 1 (1.7%) | 0
Depression | 1 (1.7%) | 0
Diplopia | 1 (1.7%) | 0
Hypersomnia | 1 (1.7%) | 0
Insomnia | 1 (1.7%) | 0
Irritability | 1 (1.7%) | 0
Nervousness | 1 (1.7%) | 0
Somnolence | 1 (1.7%) | 0

This study was too small to adequately characterize the adverse reactions leading to discontinuation. It is expected that the adverse reactions that would lead to discontinuation in this population would be similar to those resulting in discontinuation in other epilepsy trials (see tables 5 - 6).

Comparison of Gender, Age and Race - The overall adverse experience profile of LEVETIRACETAM was similar between females and males. There are insufficient data to support a statement regarding the distribution of adverse experience reports by age and race.

6.2 Postmarketing Experience

The following adverse events have been identified during postapproval use of LEVETIRACETAM. Because these events are reported voluntarily from a population of uncertain size, it is not always possible to reliably estimate their frequency or establish a casual relationship to drug exposure.

In addition to the adverse reactions listed above [see Adverse Reactions (6.1)], the following adverse events have been reported in patients receiving marketed LEVETIRACETAM worldwide.

The listing is alphabetized: abnormal liver function test, hepatic failure, hepatitis, leukopenia, neutropenia, pancreatitis, pancytopenia (with bone marrow suppression identified in some of these cases), thrombocytopenia and weight loss. Alopecia has been reported with LEVETIRACETAM use; recovery was observed in majority of cases where LEVETIRACETAM was discontinued. There have been reports of suicidal behavior (including completed suicide, suicide attempt and suicidal ideation) with marketed LEVETIRACETAM [see Patient Counseling Information (17)].

7 DRUG INTERACTIONS

7.1 General Information

In vitro data on metabolic interactions indicate that LEVETIRACETAM is unlikely to produce, or be subject to, pharmacokinetic interactions. Levetiracetam and its major metabolite, at concentrations well above Cmax levels achieved within the therapeutic dose range, are neither inhibitors of nor high affinity substrates for human liver cytochrome P450 isoforms, epoxide hydrolase or UDP-glucuronidation enzymes. In addition, levetiracetam does not affect the in vitro glucuronidation of valproic acid.

Levetiracetam circulates largely unbound (<10% bound) to plasma proteins; clinically significant interactions with other drugs through competition for protein binding sites are therefore unlikely.

Potential pharmacokinetic interactions were assessed in clinical pharmacokinetic studies (phenytoin, valproate, oral contraceptive, digoxin, warfarin, probenecid) and through pharmacokinetic screening in the placebo-controlled clinical studies in epilepsy patients.

7.2 Phenytoin

LEVETIRACETAM (3000 mg daily) had no effect on the pharmacokinetic disposition of phenytoin in patients with refractory epilepsy. Pharmacokinetics of levetiracetam were also not affected by phenytoin.

7.3 Valproate

LEVETIRACETAM (1500 mg twice daily) did not alter the pharmacokinetics of valproate in healthy volunteers. Valproate 500 mg twice daily did not modify the rate or extent of levetiracetam absorption or its plasma clearance or urinary excretion. There also was no effect on exposure to and the excretion of the primary metabolite, ucb L057.

7.4 Other Antiepileptic Drug

Potential drug interactions between LEVETIRACETAM and other AEDs (carbamazepine, gabapentin, lamotrigine, phenobarbital, phenytoin, primidone and valproate) were also assessed by evaluating the serum concentrations of levetiracetam and these AEDs during placebo-controlled clinical studies. These data indicate that levetiracetam does not influence the plasma concentration of other AEDs and that these AEDs do not influence the pharmacokinetics of levetiracetam.

7.5 Oral Contraceptives

LEVETIRACETAM (500 mg twice daily) did not influence the pharmacokinetics of an oral contraceptive containing 0.03 mg ethinyl estradiol and 0.15 mg levonorgestrel, or of the luteinizing hormone and progesterone levels, indicating that impairment of contraceptive efficacy is unlikely. Coadministration of this oral contraceptive did not influence the pharmacokinetics of levetiracetam.

7.6 Digoxin

LEVETIRACETAM (1000 mg twice daily) did not influence the pharmacokinetics and pharmacodynamics (ECG) of digoxin given as a 0.25 mg dose every day. Coadministration of digoxin did not influence the pharmacokinetics of levetiracetam.

7.7 Warfarin

LEVETIRACETAM (1000 mg twice daily) did not influence the pharmacokinetics of R and S warfarin. Prothrombin time was not affected by levetiracetam. Coadministration of warfarin did not affect the pharmacokinetics of levetiracetam.

7.8 Probenecid

Probenecid, a renal tubular secretion blocking agent, administered at a dose of 500 mg four times a day, did not change the pharmacokinetics of levetiracetam 1000 mg twice daily. Cssmax of the metabolite, ucb L057, was approximately doubled in the presence of probenecid while the fraction of drug excreted unchanged in the urine remained the same. Renal clearance of ucb L057 in the presence of probenecid decreased 60%, probably related to competitive inhibition of tubular secretion of ucb L057. The effect of LEVETIRACETAM on probenecid was not studied.

8 USE IN SPECIFIC POPULATIONS

8.1 Pregnancy

Pregnancy Category C - There are no adequate and well-controlled studies in pregnant women. In animal studies, levetiracetam produced evidence of developmental toxicity, including teratogenic effects, at doses similar to or greater than human therapeutic doses. LEVETIRACETAM should be used during pregnancy only if the potential benefit justifies the potential risk to the fetus. As with other antiepileptic drugs, physiological changes during pregnancy may affect levetiracetam concentration. There have been reports of decreased levetiracetam concentration during pregnancy. Discontinuation of antiepileptic treatments may result in disease worsening, which can be harmful to the mother and the fetus.

Administration to female rats throughout pregnancy and lactation led to increased incidences of minor fetal skeletal abnormalities and retarded offspring growth pre- and/or postnatally at doses ≥350 mg/kg/day (approximately equivalent to the maximum recommended human dose of 3000 mg [MRHD] on a mg/m^2 basis) and with increased pup mortality and offspring behavioral alterations at a dose of 1800 mg/kg/day (6 times the MRHD on a mg/m^2 basis). The developmental no effect dose was 70 mg/kg/day (0.2 times the MRHD on a mg/m^2 basis). There was no overt maternal toxicity at the doses used in this study.

There was no overt maternal toxicity at the doses used in this study.

Treatment of pregnant rabbits during the period of organogenesis resulted in increased embryofetal mortality and increased incidences of minor fetal skeletal abnormalities at doses ≥600 mg/kg/day (approximately 4 times MRHD on a mg/m^2 basis) and in decreased fetal weights and increased incidences of fetal malformations at a dose of 1800 mg/kg/day (12 times the MRHD on a mg/m^2 basis). The developmental no effect dose was 200 mg/kg/day (1.3 times the MRHD on a mg/m^2 basis). Maternal toxicity was also observed at 1800 mg/kg/day.

When pregnant rats were treated during the period of organogenesis, fetal weights were decreased and the incidence of fetal skeletal variations was increased at a dose of 3600 mg/kg/day (12 times the MRHD). 1200 mg/kg/day (4 times the MRHD) was a developmental no effect dose. There was no evidence of maternal toxici ty in this study.

Treatment of rats during the last third of gestation and throughout lactation produced no adverse developmental or maternal effects at doses of up to 1800 mg/kg/day (6 times the MRHD on a mg/m^2 basis).

Patients may enroll in the North American Antiepileptic Drug Pregnancy Registry by calling (888) 233-2334 (toll free).

8.2 Labor and Delivery

The effect of LEVETIRACETAM on labor and delivery in humans is unknown.

8.3 Nursing Mothers

Levetiracetam is excreted in breast milk. Because of the potential for serious adverse reactions in nursing infants from LEVETIRACETAM, a decision should be made whether to discontinue nursing or discontinue the drug, taking into account the importance of the drug to the mother.

8.4 Pediatric Use

Safety and effectiveness of LEVETIRACETAM injection in patients below the age of 16 years have not been established.

8.5 Geriatric Use

Of the total number of subjects in clinical studies of levetiracetam, 347 were 65 and over. No overall differences in safety were observed between these subjects and younger subjects. There were insufficient numbers of elderly subjects in controlled trials of epilepsy to adequately assess the effectiveness of LEVETIRACETAM in these patients. A study in 16 elderly subjects (age 61-88 years) with oral administration of single dose and multiple twice-daily doses for 10 days showed no pharmacokinetic differences related to age alone. Levetiracetam is known to be substantially excreted by the kidney, and the risk of adverse reactions to this drug may be greater in patients with impaired renal function. Because elderly patients are more likely to have decreased renal function, care should be taken in dose selection, and it may be useful to monitor renal function.

8.6 Use in Patients with Impaired Renal Function

Clearance of levetiracetam is decreased in patients with renal impairment and is correlated with creatinine clearance. Caution should be taken in dosing patients with moderate and severe renal impairment and in patients undergoing hemodialysis. The dosage should be reduced in patients with impaired renal function receiving LEVETIRACETAM and supplemental doses should be given to patients after dialysis [ see Clinical Pharmacology (12.3) and Dosage and Administration (2.6)].

9 DRUG ABUSE AND DEPENDENCE

The abuse and dependence potential of LEVETIRACETAM has not been evaluated in human studies.

10 OVERDOSAGE

Signs, Symptoms and Laboratory Findings of Acute Overdosage in Humans

The highest known dose of oral LEVETIRACETAM received in the clinical development program was 6000 mg/day. Other than drowsiness, there were no adverse reactions in the few known cases of overdose in clinical trials. Cases of somnolence, agitation, aggression, depressed level of consciousness, respiratory depression and coma were observed with LEVETIRACETAM overdoses in postmarketing use.

Treatment or Management of Overdose - There is no specific antidote for overdose with LEVETIRACETAM. If indicated, elimination of unabsorbed drug should be attempted by emesis or gastric lavage; usual precautions should be observed to maintain airway. General supportive care of the patient is indicated including monitoring of vital signs and observation of the patient’s clinical status. A Certified Poison Control Center should be contacted for up to date information on the management of overdose with LEVETIRACETAM.

Hemodialysis - Standard hemodialysis procedures result in significant clearance of levetiracetam (approximately 50% in 4 hours) and should be considered in cases of overdose. Although hemodialysis has not been performed in the few known cases of overdose, it may be indicated by the patient's clinical state or in patients with significant renal impairment.

11 DESCRIPTION

LEVETIRACETAM injection is an antiepileptic drug available as a clear, colorless, sterile solution (100 mg/mL) for intravenous administration.

The chemical name of levetiracetam, a single enantiomer, is (-)-(S)-α-ethyl-2-oxo-1-pyrrolidine acetamide, its molecular formula is C8H14N2O2 and its molecular weight is 170.21. Levetiracetam is chemically unrelated to existing antiepileptic drugs (AEDs). It has the following structural formula:

Levetiracetam is a white to off-white crystalline powder with a faint odor and a bitter taste. It is very soluble in water (104.0 g/100 mL). It is freely soluble in chloroform (65.3 g/100 mL) and in methanol (53.6 g/100 mL), soluble in ethanol (16.5 g/100 mL), sparingly soluble in acetonitrile (5.7 g/100 mL) and practically insoluble in n-hexane. (Solubility limits are expressed as g/100 mL solvent.)

LEVETIRACETAM injection contains 100 mg of levetiracetam per mL. It is supplied in single-use 5 mL vials containing 500 mg levetiracetam, water for injection, 45 mg sodium chloride, and buffered at approximately pH 5.5 with glacial acetic acid and 8.2 mg sodium acetate trihydrate. LEVETIRACETAM injection must be diluted prior to intravenous infusion [see Dosage and Administration (2.1)].

12 CLINICAL PHARMACOLOGY

12.1 Mechanism of Action

The precise mechanism(s) by which levetiracetam exerts its antiepileptic effect is unknown. The antiepileptic activity of levetiracetam was assessed in a number of animal models of epileptic seizures. Levetiracetam did not inhibit single seizures induced by maximal stimulation with electrical current or different chemoconvulsants and showed only minimal activity in submaximal stimulation and in threshold tests. Protection was observed, however, against secondarily generalized activity from focal seizures induced by pilocarpine and kainic acid, two chemoconvulsants that induce seizures that mimic some features of human complex partial seizures with secondary generalization. Levetiracetam also displayed inhibitory properties in the kindling model in rats, another model of human complex partial seizures, both during kindling development and in the fully kindled state. The predictive value of these animal models for specific types of human epilepsy is uncertain.

In vitro and in vivo recordings of epileptiform activity from the hippocampus have shown that levetiracetam inhibits burst firing without affecting normal neuronal excitability, suggesting that levetiracetam may selectively prevent hypersynchronization of epileptiform burst firing and propagation of seizure activity.

Levetiracetam at concentrations of up to 10μM did not demonstrate binding affinity for a variety of known receptors, such as those associated with benzodiazepines, GABA (gamma-aminobutyric acid), glycine, NMDA (N-methyl-D-aspartate), re-uptake sites, and second messenger systems. Furthermore, in vitro studies have failed to find an effect of levetiracetam on neuronal voltage-gated sodium or T-type calcium current s and levetiracetam does not appear to directly facilitate GABAergic neurotransmission. However, in vitro studies have demonstrated that levetiracetam opposes the activity of negative modulators of GABA- and glycine-gated currents and partially inhibits N-type calcium currents in neuronal cells.

A saturable and stereoselective neuronal binding site in rat brain tissue has been described for levetiracetam. Experimental data indicate that this binding site is the synaptic vesicle protein SV2A, thought to be involved in the regulation of vesicle exocytosis. Although the molecular significance of levetiracetam binding to synaptic vesicle protein SV2A is not understood, levetiracetam and related analogs showed a rank order of affinity for SV2A which correlated with the potency of their antiseizure activity in audiogenic seizure-prone mice. These findings suggest that the interaction of levetiracetam with the SV2A protein may contribute to the antiepileptic mechanism of action of the drug.

12.3 Pharmacokinetics

Equivalent doses of intravenous (IV) levetiracetam and oral levetiracetam result in equivalent Cmax, Cmin, and total systemic exposure to levetiracetam when the IV levetiracetam is administered as a 15 minute infusion.

The pharmacokinetics of levetiracetam have been studied in healthy adult subjects, adults and pediatric patients with epilepsy, elderly subjects and subjects with renal and hepatic impairment.

Overview - Levetiracetam is rapidly and almost completely absorbed after oral administration. Levetiracetam injection and tablets are bioequivalent. The pharmacokinetics of levetiracetam are linear and time-invariant, with low intra- and inter-subject variability. Levetiracetam is not significantly protein-bound (<10% bound) and its volume of distribution is close to the volume of intracellular and extracellular water. Sixty-six percent (66%) of the dose is renally excreted unchanged. The major metabolic pathway of levetiracetam (24% of dose) is an enzymatic hydrolysis of the acetamide group. It is not liver cytochrome P450 dependent. The metabolites have no known pharmacological activity and are renally excreted. Plasma half-life of levetiracetam across studies is approximately 6-8 hours. It is increased in the elderly (primarily due to impaired renal clearance) and in subjects with renal impairment.

Distribution - The equivalence of levetiracetam injection and the oral formulation was demonstrated in a bioavailability study of 17 healthy volunteers. In this study, levetiracetam 1500 mg was diluted in 100 mL 0.9% sterile saline solution and was infused over 15 minutes. The selected infusion rate provided plasma concentrations of levetiracetam at the end of the infusion period similar to those achieved at Tmax after an equivalent oral dose. It is demonstrated that levetiracetam 1500 mg intravenous infusion is equivalent to levetiracetam 3 x 500 mg oral tablets. The time independent pharmacokinetic profile of levetiracetam was demonstrated following 1500 mg intravenous infusion for 4 days with BID dosing. The AUC(0-12) at steady-state was equivalent to AUCinf following an equivalent single dose. Levetiracetam and its major metabolite are less than 10% bound to plasma proteins; clinically significant interactions with other drugs through competition for protein binding sites are therefore unlikely.

Metabolism - Levetiracetam is not extensively metabolized in humans. The major metabolic pathway is the enzymatic hydrolysis of the acetamide group, which produces the carboxylic acid metabolite, ucb L057 (24% of dose) and is not dependent on any liver cytochrome P450 isoenzymes. The major metabolite is inactive in animal seizure models. Two minor metabolites were identified as the product of hydroxylation of the 2-oxo-pyrrolidine ring (2% of dose) and opening of the 2-oxo-pyrrolidine ring in position 5 (1% of dose). There is no enantiomeric interconversion of levetiracetam or its major metabolite.

Elimination - Levetiracetam plasma half-life in adults is 7 ± 1 hour and is unaffected by either dose, route of administration or repeated administration. Levetiracetam is eliminated from the systemic circulation by renal excretion as unchanged drug which represents 66% of administered dose. The total body clearance is 0.96 mL/min/kg and the renal clearance is 0.6 mL/min/kg. The mechanism of excretion is glomerular filtration with subsequent partial tubular reabsorption. The metabolite ucb L057 is excreted by glomerular filtration and active tubular secretion with a renal clearance of 4 mL/min/kg. Levetiracetam elimination is correlated to creatinine clearance. Levetiracetam clearance is reduced in patients with impaired renal function [see Use in Specific Populations (8.6) and Dosage and Administration (2.6)].

Pharmacokinetic Interactions - In vitro data on metabolic interactions indicate that levetiracetam is unlikely to produce, or be subject to, pharmacokinetic interactions. Levetiracetam and its major metabolite, at concentrations well above Cmax levels achieved within the therapeutic dose range, are neither inhibitors of, nor high affinity substrates for, human liver cytochrome P450 isoforms, epoxide hydrolase or UDP-glucuronidation enzymes. In addition, levetiracetam does not affect the in vitro glucuronidation of valproic acid.

Potential pharmacokinetic interactions of or with levetiracetam were assessed in clinical pharmacokinetic studies (phenytoin, valproate, warfarin, digoxin, oral contraceptive, probenecid) and through pharmacokinetic screening in the placebo-controlled clinical studies in epilepsy patients [see Drug Interactions (7)].

Special Populations

Elderly - Pharmacokinetics of levetiracetam were evaluated in 16 elderly subjects (age 61 to 88 years) with creatinine clearance ranging from 30 to 74 mL/min. Following oral administration of twice-daily dosing for 10 days, total body clearance decreased by 38% and the half-life was 2.5 hours longer in the elderly compared to healthy adults. This is most likely due to the decrease in renal function in these subjects.

Pediatric Patients - Safety and effectiveness of LEVETIRACETAM injection in patients below the age of 16 years have not been established

Gender - Levetiracetam Cmax and AUC were 20% higher in women (N=11) compared to men (N=12). However, clearances adjusted for body weight were comparable.

Race - Formal pharmacokinetic studies of the effects of race have not been conducted. Cross study comparisons involving Caucasians (N=12) and Asians (N=12), however, show that pharmacokinetics of levetiracetam were comparable between the two races. Because levetiracetam is primarily renally excreted and there are no important racial differences in creatinine clearance, pharmacokinetic differences due to race are not expected.

Renal Impairment - The disposition of levetiracetam was studied in adult subjects with varying degrees of renal function. Total body clearance of levetiracetam is reduced in patients with impaired renal function by 40% in the mild group (CLcr = 50 to 80 mL/min), 50% in the moderate group (CLcr = 30 to 50 mL/min) and 60% in the severe renal impairment group (CLcr <30 mL/min). Clearance of levetiracetam is correlated with creatinine clearance.

In anuric (end stage renal disease) patients, the total body clearance decreased 70% compared to normal subjects (CLcr >80mL/min). Approximately 50% of the pool of levetiracetamin the body is removed during a standard 4 hour hemodialysis procedure.

Dosage should be reduced in patients with impaired renal function receiving levetiracetam, and supplemental doses should be given to patients after dialysis [see Dosage and Administration (2.6)].

Hepatic Impairment - In subjects with mild (Child-Pugh A) to moderate (Child-Pugh B) hepatic impairment, the pharmacokinetics of levetiracetam were unchanged. In patients with severe hepatic impairment (Child-Pugh C), total body clearance was 50% that of normal subjects, but decreased renal clearance accounted for most of the decrease. No dose adjustment is needed for patients with hepatic impairment.

13 NONCLINICAL TOXICOLOGY

13.1 Carcinogenesis, Mutagenesis, Impairment of Fertility

Carcinogenesis - Rats were dosed with levetiracetam in the diet for 104 weeks at doses of 50, 300 and 1800 mg/kg/day. The highest dose corresponds to 6 times the maximum recommended daily human dose (MRHD) of 3000 mg on a mg/m^2 basis and it also provided systemic exposure (AUC) approximately 6 times that achieved in humans receiving the MRHD. There was no evidence of carcinogenicity. A study was conducted in which mice received levetiracetam in the diet for 80 weeks at doses of 60, 240 and 960 mg/kg/day (high dose is equivalent to 2 times the MRHD on a mg/m^2 or exposure basis). Although no evidence for carcinogenicity was seen, the potential for a carcinogenic response has not been fully evaluated in that species because adequate doses have not been studied.

Mutagenesis - Levetiracetam was not mutagenic in the Ames test or in mammalian cells in vitro in the Chinese hamster ovary/HGPRT locus assay. It was not clastogenic in an in vitro analysis of metaphase chromosomes obtained from Chinese hamster ovary cells or in an in vivo mouse micronucleus assay. The hydrolysis product and major human metabolite of levetiracetam (ucb L057) was not mutagenic in the Ames test or the in vitro mouse lymphoma assay.

Impairment of Fertility - No adverse effects on male or female fertility or reproductive performance were observed in rats at doses up to 1800 mg/kg/day (approximately 6 times the maximum recommended human dose on a mg/m^2 or exposure basis).

13.2 Animal Pharmacology and/or Toxicology

ln animal studies, levetiracetam produced evidence of developmental toxicity at doses similar to or greater than human therapeutic doses.

14 CLINICAL STUDIES

All efficacy trials utilized oral formulations. The recommendation for the parenteral formulation is based upon these studies as well as the demonstration of comparable bioavailability of the oral and the parenteral formulation [see Pharmacokinetics (12.3)].

In the following studies, statistical significance versus placebo indicates a p value < 0.05.

14.1 Partial Onset Seizures

Effectiveness in Partial Onset Seizures in Adults with Epilepsy -The effectiveness of LEVETIRACETAM as adjunctive therapy (added to other antiepileptic drugs) in adults was established in three multicenter, randomized, double-blind, placebo-controlled clinical studies in patients who had refractory partial onset seizures with or without secondary generalization. The tablet formulation was used in all these studies. In these studies, 904 patients were randomized to placebo, 1000 mg, 2000 mg, or 3000 mg/day. Patients enrolled in Study 1 or Study 2 had refractory partial onset seizures for at least two years and had taken two or more classical AEDs. Patients enrolled in Study 3 had refractory partial onset seizures for at least 1 year and had taken one classical AED. At the time of the study, patients were taking a stable dose regimen of at least one and could take a maximum of two AEDs. During the baseline period, patients had to have experienced at least two partial onset seizures during each 4-week period.

The criteria for statistical significance in all studies was a p value < 0.05.

Study 1

Study 1 was a double-blind, placebo-controlled, parallel-group study conducted at 41 sites in the United States comparing LEVETIRACETAM 1000 mg/day (N=97), LEVETIRACETAM 3000 mg/day (N=101), and placebo (N=95) given in equally divided doses twice daily. After a prospective baseline period of 12 weeks, patients were randomized to one of the three treatment groups described above. The 18-week treatment period consisted of a 6-week titration period, followed by a 12-week fixed dose evaluation period, during which concomitant AED regimens were held constant. The primary measure of effectiveness was a between group comparison of the percent reduction in weekly partial seizure frequency relative to placebo over the entire randomized treatment period (titration + evaluation period). Secondary outcome variables included the responder rate (incidence of patients with ≥50% reduction from baseline in partial onset seizure frequency). The results of the analysis of Study 1 are displayed in Table 7.

Table 7: Reduction in Mean Over Placebo in Weekly Frequency of Partial Onset Seizures in Study 1
 | Placebo | LEVETIRACETAM | LEVETIRACETAM
 | (N=95) | 1000 mg/day | 3000 mg/day
 |  | (N=97) | (N=101)
Percent reduction in partial seizure frequency over placebo | - | 26.1%* | 30.1%*
* Statistically significant versus placebo

The percentage of patients (y-axis) who achieved ≥50% reduction in weekly seizure rates from baseline in partial onset seizure frequency over the entire randomized treatment period (titration + evaluation period) within the three treatment groups (x-axis) is presented in Figure 1.

Figure 1: Responder Rate (≥50% Reduction from Baseline) in Study 1

* Statistically significant versus placebo

Study 2 - Study 2 was a double-blind, placebo-controlled, crossover study conducted at 62 centers in Europe comparing LEVETIRACETAM 1000 mg/day (N=106), LEVETIRACETAM 2000 mg/day (N=105), and placebo (N=111) given in equally divided doses twice daily.

The first period of the study (Period A) was designed to be analyzed as a parallel-group study. After a prospective baseline period of up to 12 weeks, patients were randomized to one of the three treatment groups described above. The 16-week treatment period consisted of the 4-week titration period followed by a 12-week fixed dose evaluation period, during which concomitant AED regimens were held constant. The primary measure of effectiveness was a between group comparison of the percent reduction in weekly partial seizure frequency relative to placebo over the entire randomized treatment period (titration + evaluation period). Secondary outcome variables included the responder rate (incidence of patients with ≥50% reduction from baseline in partial onset seizure frequency). The results of the analysis of Period A are displayed in Table 8.

Table 8: Reduction in Mean Over Placebo in Weekly Frequency of Partial Onset Seizures in Study 2: Period A
 | Placebo | LEVETIRACETAM | LEVETIRACETAM
 |  | 1000 mg/day | 2000 mg/day
 | (N=111) | (N=106) | (N=105)
Percent reduction in partial seizure frequency over placebo | - | 17.1%* | 21.4%*
* Statistically significant versus placebo

The percentage of patients (y-axis) who achieved ≥50% reduction in weekly seizure rates from baseline in partial onset seizure frequency over the entire randomized treatment period (titration + evaluation period) within the three treatment groups (x-axis) is presented in Figure 2.

Figure 2: Responder Rate (≥50% Reduction from Baseline) in Study 2: Period A

* Statistically significant versus placebo

The comparison of LEVETIRACETAM 2000 mg/day to LEVETIRACETAM 1000 mg/day for responder rate was statistically significant (P=0.02). Analysis of the trial as a cross-over yielded similar results.

Study 3

Study 3 was a double-blind, placebo-controlled, parallel-group study conducted at 47 centers in Europe comparing LEVETIRACETAM 3000 mg/day (N=180) and placebo (N=104) in patients with refractory partial onset seizures, with or without secondary generalization, receiving only one concomitant AED. Study drug was given in two divided doses. After a prospective baseline period of 12 weeks, patients were randomized to one of two treatment groups described above. The 16-week treatment period consisted of a 4-week titration period, followed by a 12-week fixed dose evaluation period, during which concomitant AED doses were held constant. The primary measure of effectiveness was a between group comparison of the percent reduction in weekly seizure frequency relative to placebo over the entire randomized treatment period (titration + evaluation period). Secondary outcome variables included the responder rate (incidence of patients with ≥50% reduction from baseline in partial onset seizure frequency). Secondary outcome variables included the responder rate (incidence of patients with ≥50% reduction from baseline in partial onset seizure frequency). Table 9 displays the results of the analysis of Study 3.

Table 9: Reduction in Mean Over Placebo in Weekly Frequency of Partial Onset Seizures in Study 3
 | Placebo | LEVETIRACETAM
 |  | 3000 mg/day
 | (N=104) | (N=180)
Percent reduction in partial seizure frequency over placebo | - | 23.0%*
* Statistically significant versus placebo

The percentage of patients (y-axis) who achieved ≥50% reduction in weekly seizure rates from baseline in partial onset seizure frequency over the entire randomized treatment period (titration + evaluation period) within the two treatment groups (x-axis) is presented in Figure 3.

Figure 3: Responder Rate (≥50% Reduction from Baseline) in Study 3

* Statistically significant versus placebo

14.2 Myoclonic Seizures in Patients with Juvenile Myoclonic Epilepsy

Effectiveness in Myoclonic Seizures in Patients with Juvenile Myoclonic Epilepsy (JME)

The effectiveness of LEVETIRACETAM as adjunctive therapy (added to other antiepileptic drugs) in patients with juvenile myoclonic epilepsy (JME) experiencing myoclonic seizures was established in one multicenter, randomized, double-blind, placebo-controlled study, conducted at 37 sites in 14 countries. Of the 120 patients enrolled, 113 had a diagnosis of confirmed or suspected JME. Eligible patients on a stable dose of 1 antiepileptic drug (AED) experiencing one or more myoclonic seizures per day for at least 8 days during the prospective 8-week baseline period were randomized to either LEVETIRACETAM or placebo (LEVETIRACETAM N=60, placebo N=60). Patients were titrated over 4 weeks to a target dose of 3000 mg/day and treated at a stable dose of 3000 mg/day over 12 weeks (evaluation period). Study drug was given in 2 divided doses.

The primary measure of effectiveness was the proportion of patients with at least 50% reduction in the number of days per week with one or more myoclonic seizures during the treatment period (titration + evaluation periods) as compared to baseline. Table 10 displays the results for the 113 patients with JME in this study.

Table 10: Responder Rate (≥50% Reduction from Baseline) in Myoclonic Seizure Days per Week for Patients with JME
 | Placebo | LEVETIRACETAM
 | (N=59) | (N=54)
Percentage of responders | 23.7% | 60.4%*
* Statistically significant versus placebo

16 HOW SUPPLIED/STORAGE AND HANDLING

16.1 How Supplied

LEVETIRACETAM (500 mg/5 mL injection is a clear, colorless, sterile solution. It is supplied in single-use 5 mL vials, available in cartons of 10 vials (NDC 14789-400-05).

16.2 Storage

Store at 25°C (77°F); excursions permitted to 15 to 30°C (59 to 86°F) [see USP Controlled Room Temperature].

17 PATIENT COUNSELING INFORMATION

Patients should be advised to notify their physician if they are pregnant prior to therapy.

Patients should be advised that LEVETIRACETAM may cause dizziness and somnolence. Accordingly, patients should be advised not to drive or operate heavy machinery or engage in other hazardous activities until they have gained sufficient experience on LEVETIRACETAM to gauge whether it adversely affects their performance of these activities.

Patients should be advised that LEVETIRACETAM may cause changes in behavior (e.g. aggression, agitation, anger, anxiety, apathy , depression, hostility, and irritability) and in rare cases patients may experience psychotic symptoms.

Patients should be advised to immediately report any symptoms of depression and/or suicidal ideation to their prescribing physician as suicide, suicide attempt and suicidal ideation have been reported in patients treated with levetiracetam.

LEVETIRACETAM Injection is manufactured in the USA for Nexus Pharmaceuticals Inc., Vernon Hills, IL 60061

PACKAGE LABEL

Levetiracetam Injection 10 Single Use 5 mL vials Box

NDC 14789-400-05

10 Single Use 5 mL vials

Levetiracetam Injection
500 mg/ 5mL (100 mg/mL)

Rx only

FOR INTRAVENOUS USE ONLY

MUST BE DILUTED PRIOR TO ADMINISTRATION